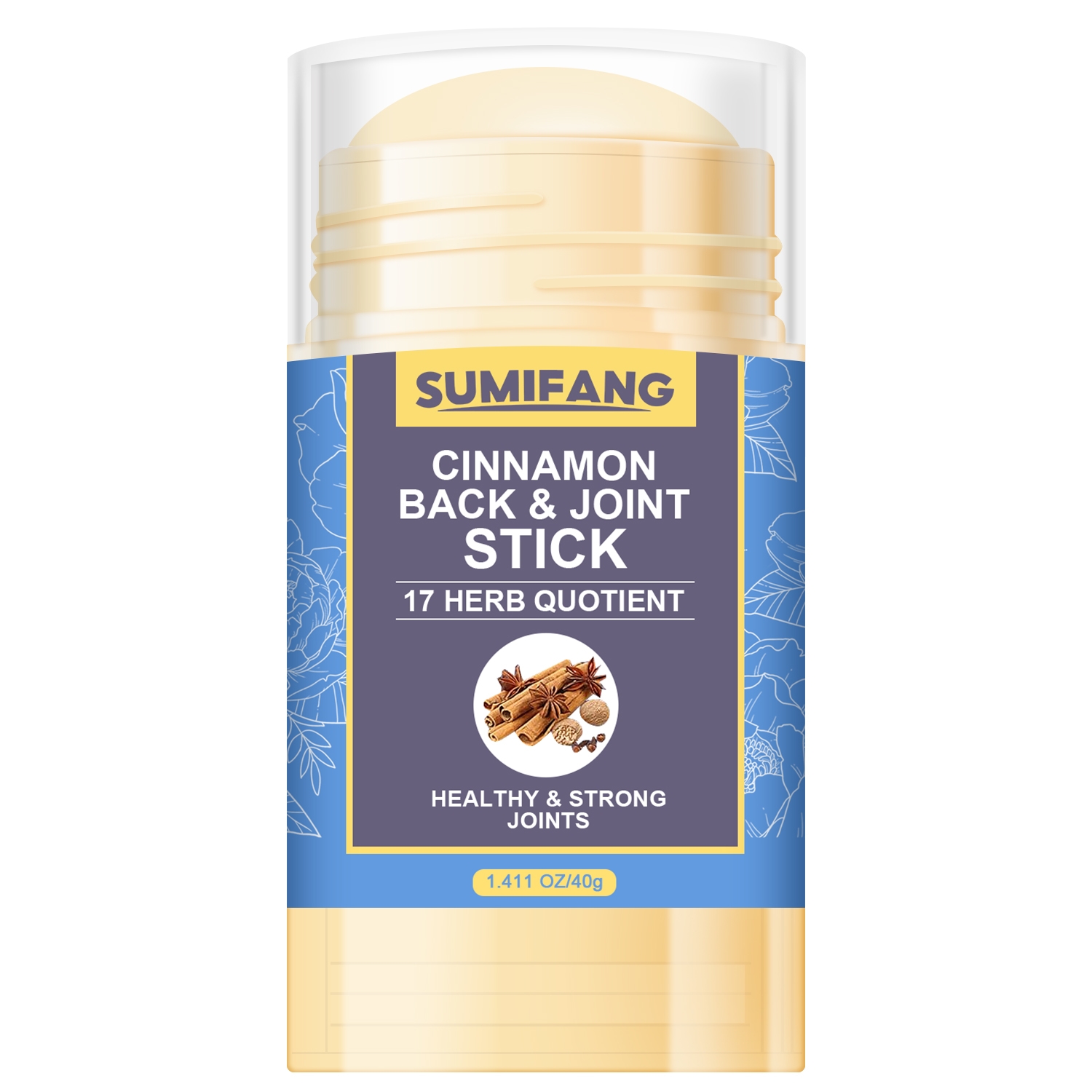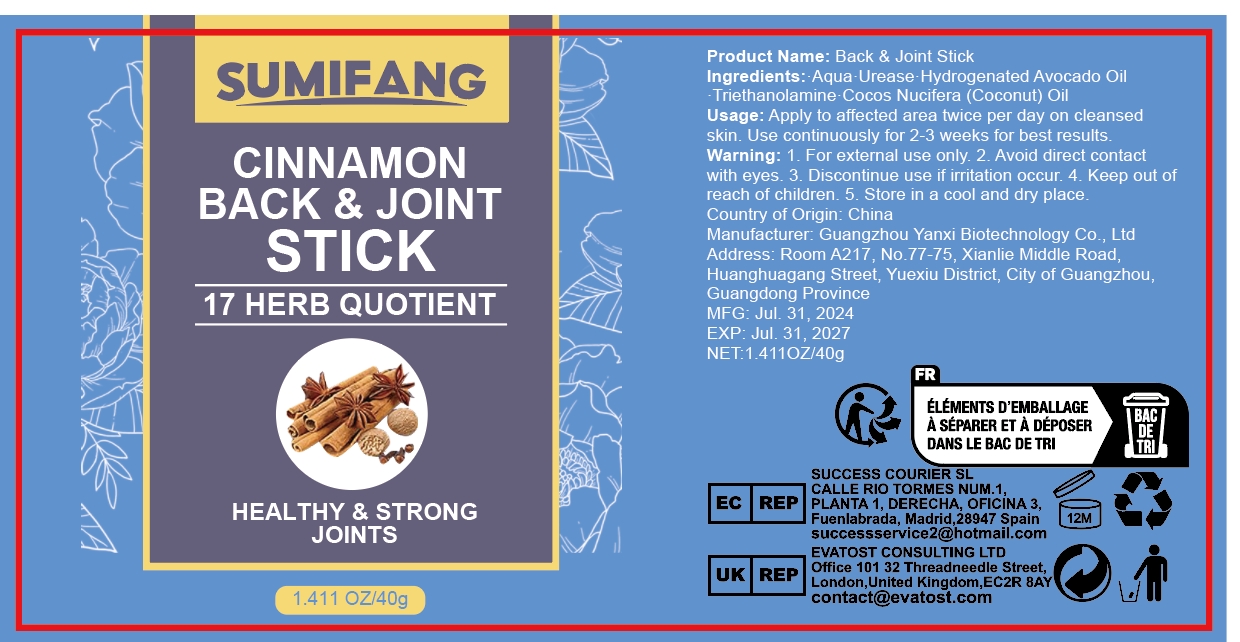 DRUG LABEL: BACK JOINTSTICK
NDC: 84025-109 | Form: STICK
Manufacturer: Guangzhou Yanxi Biotechnology Co.. Ltd
Category: otc | Type: HUMAN OTC DRUG LABEL
Date: 20240801

ACTIVE INGREDIENTS: HYDROGENATED AVOCADO OIL 5 mg/40 g; CUPRIC TRIETHANOLAMINE 3 mg/40 g
INACTIVE INGREDIENTS: WATER

DOSAGE AND ADMINISTRATION

stick for moisturizing and massaging the back and joints

WARNINGS

Keep out of children

INACTIVE INGREDIENT

Aqua

INDICATIONS AND USAGE

For daily skin care

keep out of children

PURPOSE

Massages and moisturizes the back